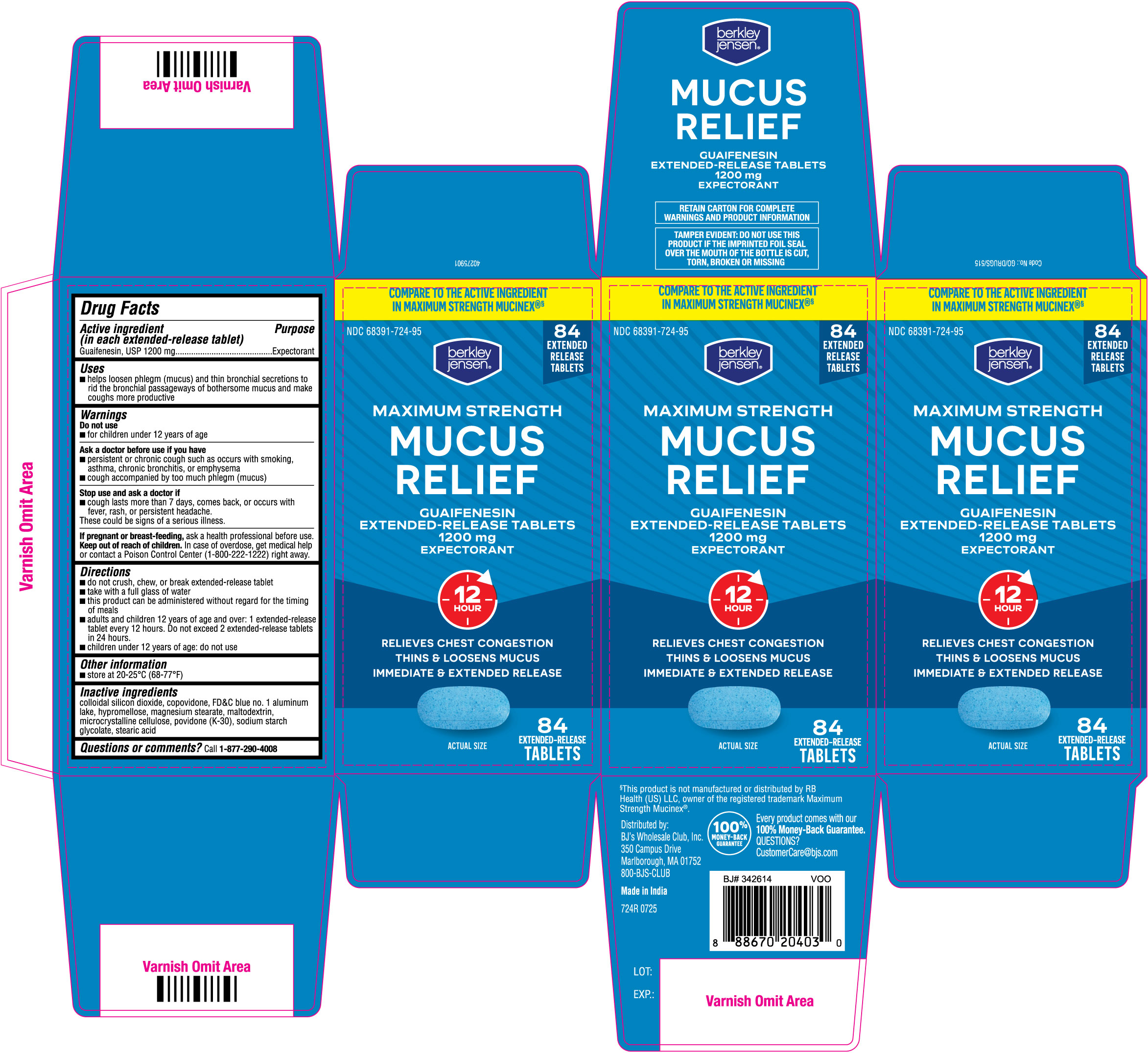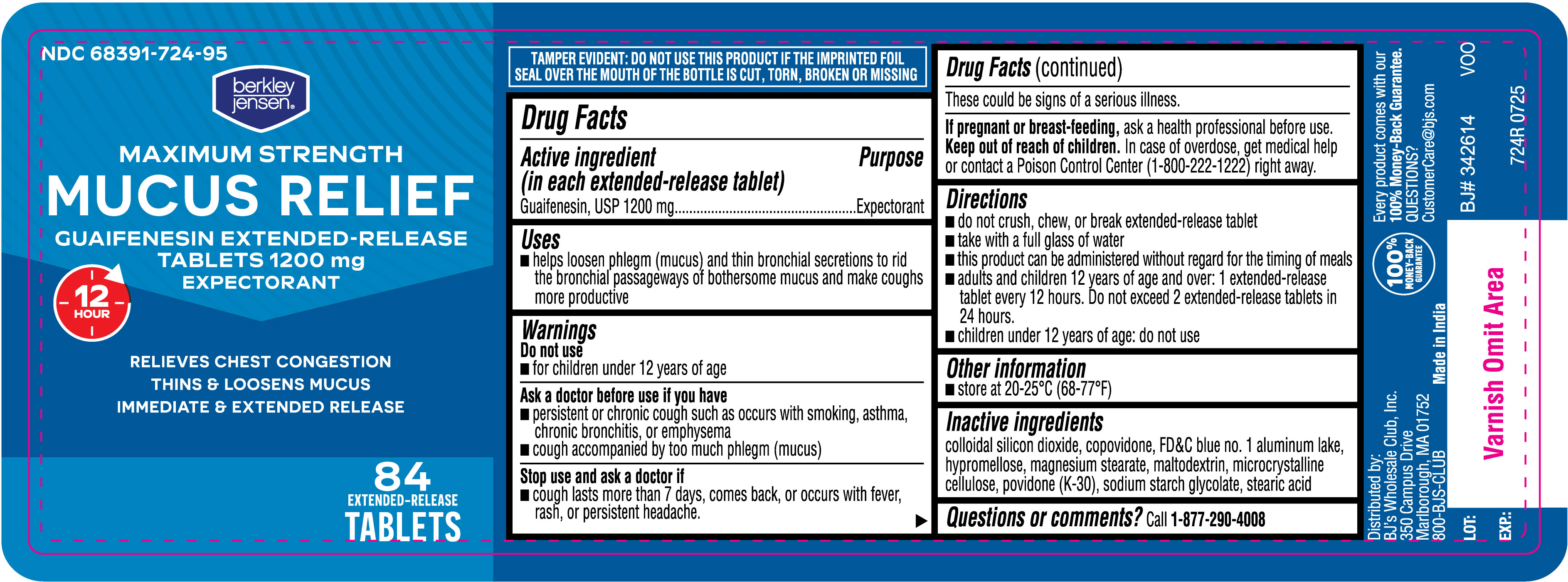 DRUG LABEL: Mucus Relief
NDC: 68391-724 | Form: TABLET, EXTENDED RELEASE
Manufacturer: BJWC (Berkley & Jensen / BJ's)
Category: otc | Type: HUMAN OTC DRUG LABEL
Date: 20250819

ACTIVE INGREDIENTS: GUAIFENESIN 1200 mg/1 1
INACTIVE INGREDIENTS: STEARIC ACID; MICROCRYSTALLINE CELLULOSE; COPOVIDONE K25-31; FD&C BLUE NO. 1 ALUMINUM LAKE; HYPROMELLOSE, UNSPECIFIED; POVIDONE K30; SODIUM STARCH GLYCOLATE TYPE A; SILICON DIOXIDE; MAGNESIUM STEARATE; MALTODEXTRIN

BJs Guaifenesin Extended Release Tablets 1200 mg

Drug Facts

Active ingredient (in each extended-release tablet)

Guaifenesin, USP 1200 mg

Purpose

Expectorant

Uses

- helps loosen phlegm (mucus) and thin bronchial secretions to rid the bronchial passageways of bothersome mucus and make coughs more productive

Warnings

Do not use

- for children under 12 years of age

Ask a doctor before use if you have

- persistent or chronic cough such as occurs with smoking, asthma, chronic bronchitis, or emphysema
- cough accompanied by too much phlegm (mucus)

Stop use and ask a doctor if

- cough lasts more than 7 days, comes back, or occurs with fever, rash, or persistent headache. These could be signs of a serious illness.

PREGNANCY OR BREAST FEEDING

If pregnant or breast-feeding, ask a health professional before use.

Keep out of reach of children. In case of overdose, get medical help or contact a Poison Control Center (1-800-222-1222) right away.

Directions

- do not crush, chew, or break extended-release tablet
- take with a full glass of water
- this product can be administered without regard for the timing of meals
- adults and children 12 years of age and over: 1 extended-release tablet every 12 hours. Do not exceed 2 extended-release tablets in 24 hours.
- children under 12 years of age: do not use

Other information

- store at 20-25°C (68-77°F)

INACTIVE INGREDIENT

Inactive ingredients colloidal silicon dioxide, copovidone, FD&C blue no. 1 aluminum lake, hypromellose, magnesium stearate, maltodextrin, microcrystalline cellulose, povidone (K-30), sodium starch glycolate, stearic acid.

Questions or comments? Call 1-877-290-4008

724R 84ct label

724R 84ct Carton